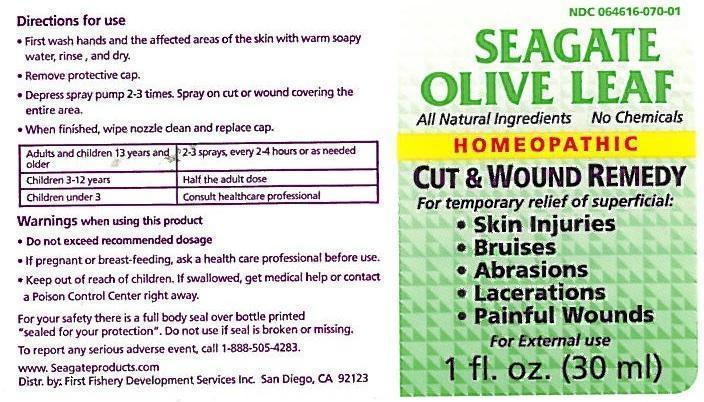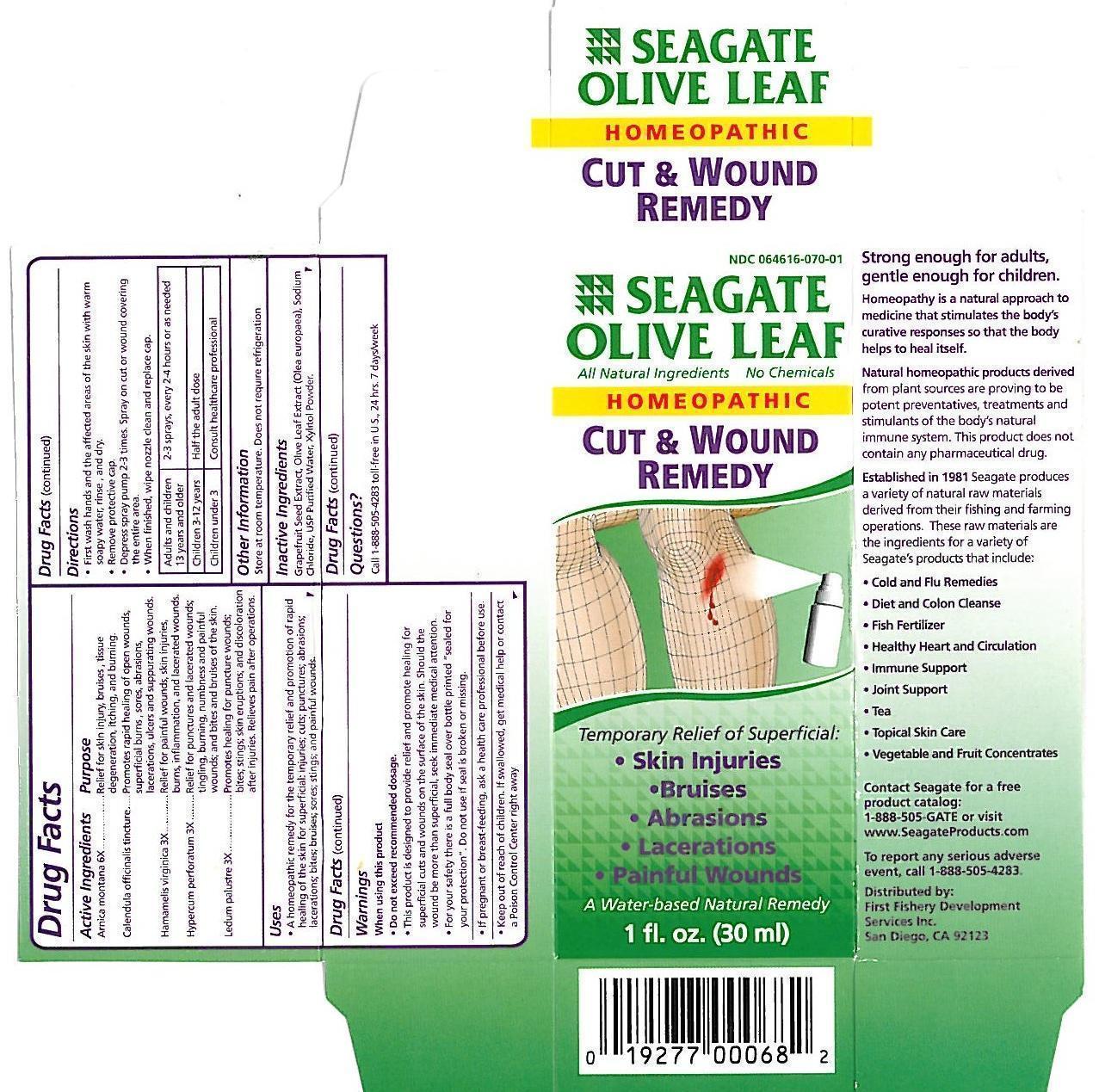 DRUG LABEL: Cut and Wound Remedy
NDC: 64616-070 | Form: SPRAY
Manufacturer: Vitality Works, Inc.
Category: homeopathic | Type: HUMAN OTC DRUG LABEL
Date: 20171206

ACTIVE INGREDIENTS: ARNICA MONTANA 6 [hp_X]/1 mL; CALENDULA OFFICINALIS FLOWERING TOP 1 [hp_X]/1 mL; HAMAMELIS VIRGINIANA ROOT BARK/STEM BARK 3 [hp_X]/1 mL; HYPERICUM PERFORATUM 3 [hp_X]/1 mL; LEDUM PALUSTRE TWIG 3 [hp_X]/1 mL
INACTIVE INGREDIENTS: CITRUS PARADISI SEED; OLEA EUROPAEA LEAF; SODIUM CHLORIDE; WATER; XYLITOL

Olive Leaf Cut & Wound Remedy Spray

Olive Leaf Cut & Wound Remedy

Arnica montana 6X

Calendula officinalis 1X

Hamamelis virginica 3X

Hypericum perforatum 3X

Ledum palustre 3X

Olive Leaf Cut & Wound Remedy

Grapefruit Seed Extract, Olive Leaf Extract (Olea europaea), Sodium Chloride, USP Purified Water, Xylitol powder.

Olive Leaf Cut & Wound Remedy

-Do not exceed recommended dosage.

-This product is designed to provide relief and promote healing for superficial cuts and wounds on the surface of the skin. Should the wound be more than superficial seek immediate medical attention.

-For your safety there is a full body seal over bottle printed "sealed for you protection". Do not use if seal is broken or missing.

Olive Leaf Cut & Wound Remedy

Keep out of reach of children. If swallowed, get medical help or contact a Poison Control Center right away.

Olive Leaf Cut & Wound Remedy

A homeopathic remedy for the temporary relief and promotion of rapid healing of the skin for superficial injuries, cuts, punctures, abrasions, lacerations, bites, bruises, sores, stings, and painful wounds.

Olive Leaf Cut & Wound Remedy

-First wash hands and the affected areas of the skin with warm soapy water, rinse and dry.

-Remove protective cap.

-Depress spray pump 2-3 times. Spray on cut or wound covering the entire area.

-When finished wipe nozzle clean and replace cap.

Adults and children 13 years and older - 2-3 sprays, every 2-4 hours or as needed.

Children 3-12 years - Half the adult dose

Children under 3 - Consult healthcare professional

Olive Leaf Cut & Wound Remedy

Arnica montana - Relief for skin injury, bruises, tissue.

Caledula officinalis - Promotes rapid healing of open wounds, superficial burns, sores, abrasions, lacerations, ulcers and suppurating wounds

Hamamelis viginica - Relief for painful wounds, skin injuries, burns, inflammation, and lacerated wounds.

Hypericum perforatum - Relief for punctures and lacerated wounds; tingling, burning, numbness and painful wounds; and bites and bruises of the skin.

Ledum palustre - Promotes healing for puncture wounds; bites, stings, skin eruptions; and discoloration after injuries. Relieves pain after operations.